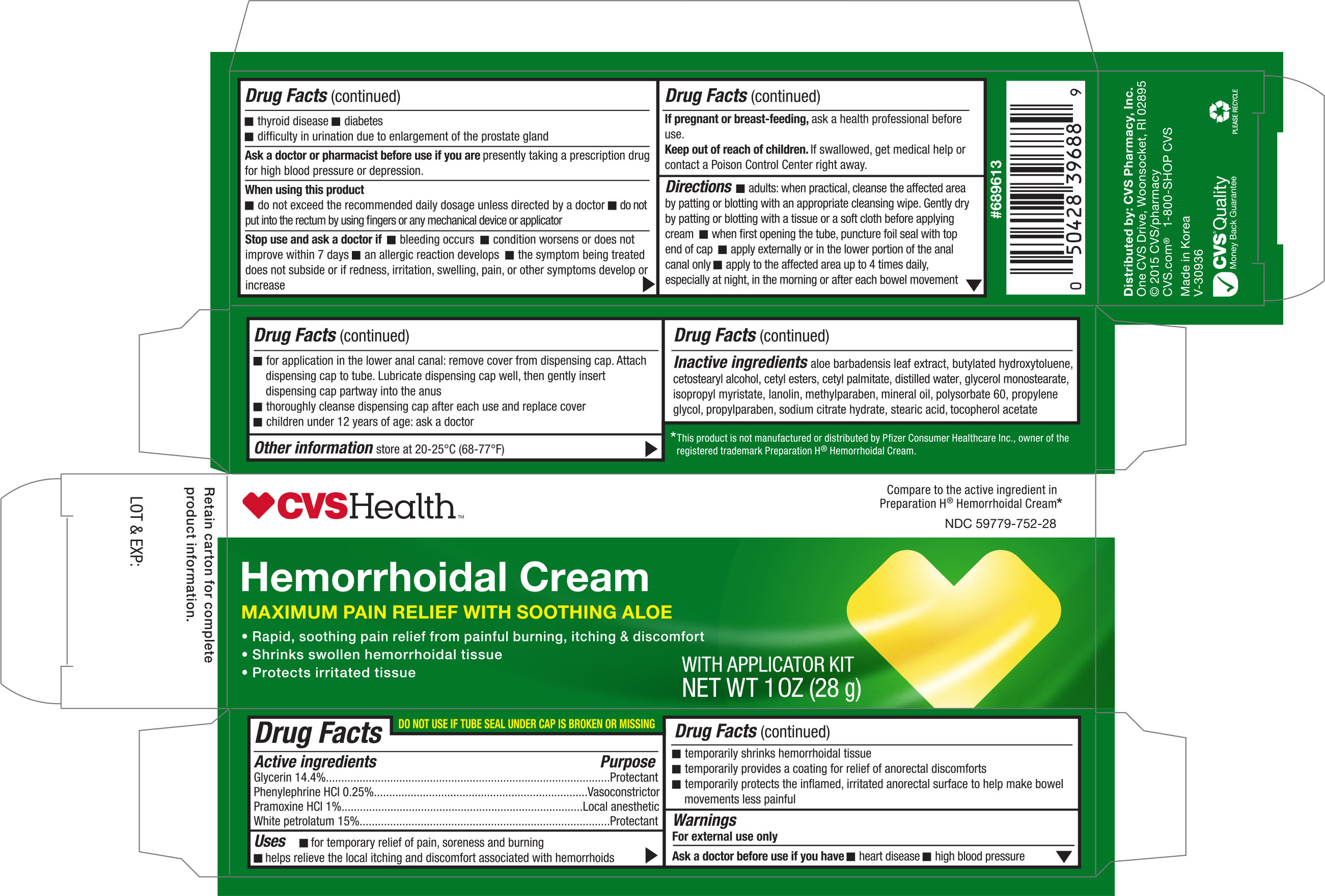 DRUG LABEL: CVS Hemorrhoidal
NDC: 59779-752 | Form: CREAM
Manufacturer: CVS Pharmacy, Inc.
Category: otc | Type: HUMAN OTC DRUG LABEL
Date: 20181221

ACTIVE INGREDIENTS: GLYCERIN 14.4 g/100 g; PHENYLEPHRINE HYDROCHLORIDE 0.25 g/100 g; PRAMOXINE HYDROCHLORIDE 1 g/100 g; PETROLATUM 15 g/100 g
INACTIVE INGREDIENTS: ALOE VERA LEAF; BUTYLATED HYDROXYTOLUENE; CETOSTEARYL ALCOHOL; CETYL ESTERS WAX; CETYL PALMITATE; WATER; GLYCERYL MONOSTEARATE; ISOPROPYL MYRISTATE; LANOLIN; METHYLPARABEN; MINERAL OIL; POLYSORBATE 60; PROPYLENE GLYCOL; PROPYLPARABEN; TRISODIUM CITRATE DIHYDRATE; STEARIC ACID; ALPHA-TOCOPHEROL ACETATE

CVS Hemorrhoidal Cream 1oz (with applicator) (48175, 2018)

Active Ingredients Purpose

Glycerin 14.4%...................................... Protectant

Phenylephrine HCI 0.25%........................ Vasoconstrictor

Pramoxine HCI 1%..................................Local anesthetic

White Petrolatum 15%.............................Protectant

Uses

- For temporary relief of pain, soreness and burning
- Helps relieve the local itching and discomfort associated with hemorrhoids
- Temporarily shrinks hemorrhoidal tissue
- Temporarily provides a coating for relief of anorectal discomforts
- Temporarily protects the inflamed, irritaed anorectal surface to help make bowel movements less painful

Warnings

For external use only

Ask a doctor before use if you have

- heart disease
- high blood pressure
- Thyroid disease
- Diabetes
- Difficulty in urination due to enlargement of the prostate gland

Ask a doctor or pharmacist before use if you are presently taking a prescription drug for high blood pressure or depression

When using this product

- Do not exceed the recommended daily dosage unless directed by a doctor
- Do not put into rectum by using fingers or any mechanical device or applicator

PREGNANCY OR BREAST FEEDING

If pregnant or breast-feeding, ask a health professional before use.

Keep out of reach of children. If swallowed, get medical help or contact a Poision Control Center right away.

Directions

- Adults: when practical, cleanse the affected area by patting or blottign with an appropriate cleansing wipe. Gently dry by patting or blotting with a tissue or a soft cloth before applying.
- When first opening the tube, puncture foil seal with top end of cap
- Apply externally or in the lower portion of the anal canal only
- Apply to the affected area up to 4 times daily, especially at night, in the morning or after each bowel movement
- For application in the lower anal canal: remove cover from dispensing cap. Attach dispensing cap to tube, lubricate dispensing cap well, then gently insert dispensing cap partway into the anus.
- Thoroughly cleanse dispensing cap after each use and replace cover.
- Children under 12 years of age: ask a doctor

Other Information

store at 20-25°C (68-77°F)

Inactive ingredients

aloe barbadensis leaf extract, butylated hydroxytoluene, cetosteraly alcohol, cetyl esters, cetyl palmitate, distilled water, glycerol monostearate, isopropyl myristate, lanolin, methylparaben, mineral oil, polysorbate 60, propylene glycol, propylparaben, sodium citrate hydrate, stearic acid, tocopherol acetate

DOSAGE AND ADMINISTRATION

DISTRIBUTED BY:

CVS PHARMACY, INC.

ONE CVS DRIVE

WOONSOCKET, RI 02895 USA